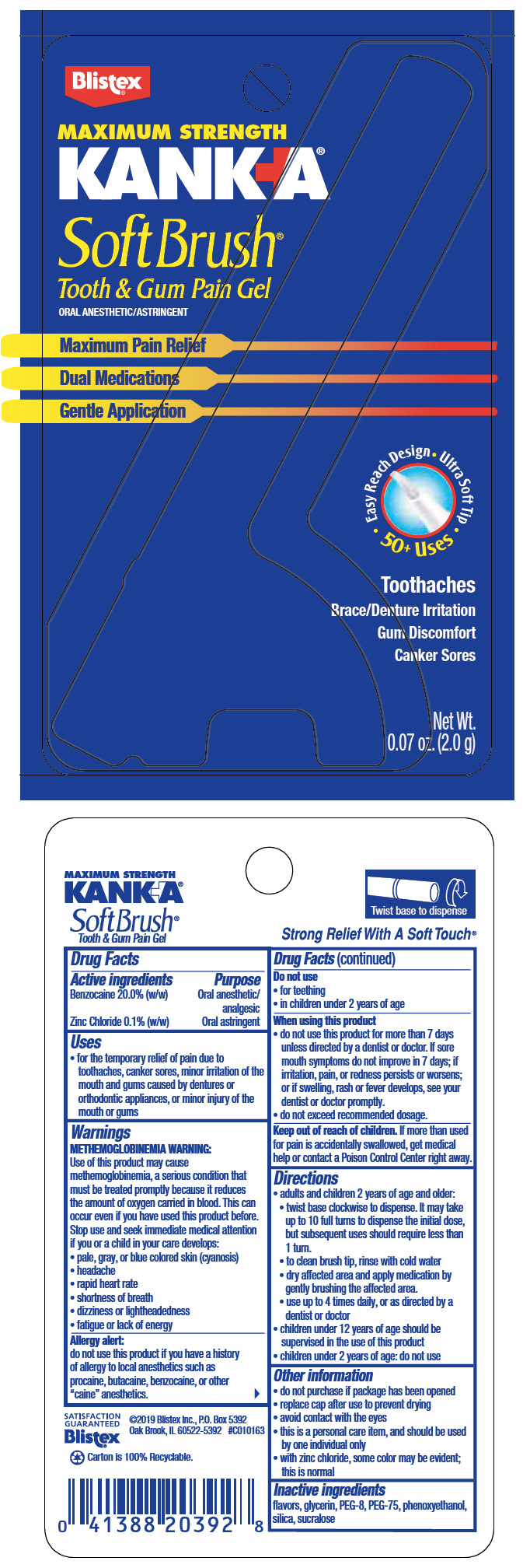 DRUG LABEL: KANKA 
NDC: 10157-2106 | Form: GEL
Manufacturer: Blistex Inc
Category: otc | Type: HUMAN OTC DRUG LABEL
Date: 20241212

ACTIVE INGREDIENTS: BENZOCAINE 20 mg/100 g; ZINC CHLORIDE 0.1 g/100 g
INACTIVE INGREDIENTS: POLYETHYLENE GLYCOL 400; POLYETHYLENE GLYCOL 3350; GLYCERIN; SUCRALOSE; PHENOXYETHANOL; SILICON DIOXIDE

KANKA®
SoftBrush

Drug Facts

ACTIVE INGREDIENT

Active ingredients | Purpose
Benzocaine 20.0% (w/w) | Oral anesthetic/analgesic
Zinc Chloride 0.1% (w/w) | Oral astringent

Uses

- for the temporary relief of pain due to toothaches, canker sores, minor irritation of the mouth and gums caused by dentures or orthodontic appliances, or minor injury of the mouth or gums

Warnings

METHEMOGLOBINEMIA WARNING

Use of this product may cause methemoglobinemia, a serious condition that must be treated promptly because it reduces the amount of oxygen carried in blood. This can occur even if you have used this product before. Stop use and seek immediate medical attention if you or a child in your care develops:

- pale, gray, or blue colored skin (cyanosis)
- headache
- rapid heart rate
- shortness of breath
- dizziness or lightheadedness
- fatigue or lack of energy

Allergy alert: do not use this product if you have a history of allergy to local anesthetics such as procaine, butacaine, benzocaine, or other "caine" anesthetics.

Do not use

- for teething
- in children under 2 years of age

When using this product

- do not use this product for more than 7 days unless directed by a dentist or doctor. If sore mouth symptoms do not improve in 7 days; if irritation, pain, or redness persists or worsens; or if swelling, rash or fever develops, see your dentist or doctor promptly.
- do not exceed recommended dosage.

Keep out of reach of children. If more than used for pain is accidentally swallowed, get medical help or contact a Poison Control Center right away.

Directions

- adults and children 2 years of age and older:
  - twist base clockwise to dispense. It may take up to 10 full turns to dispense the initial dose, but subsequent uses should require less than 1 turn.
  - to clean brush tip, rinse with cold water
  - dry affected area and apply medication by gently brushing the affected area.
  - use up to 4 times daily, or as directed by a dentist or doctor
- children under 12 years of age should be supervised in the use of this product
- children under 2 years of age: do not use

Other information

- do not purchase if package has been opened
- replace cap after use to prevent drying
- avoid contact with the eyes
- this is a personal care item, and should be used by one individual only
- with zinc chloride, some color may be evident; this is normal

Inactive ingredients

flavors, glycerin, PEG-8, PEG-75, phenoxyethanol, silica, sucralose

PRINCIPAL DISPLAY PANEL - 2.0 g Applicator Blister Pack

Blistex®

MAXIMUM STRENGTH
KANKA®

Soft Brush®
Tooth & Gum Pain Gel
ORAL ANESTHETIC/ASTRINGENT

Maximum Pain Relief

Dual Medications

Gentle Application

Easy Reach Design
Ultra Soft Tip
50+ Uses

Toothaches
Brace/Denture Irritation
Gum Discomfort
Canker Sores

Net Wt.
0.07 oz. (2.0 g)